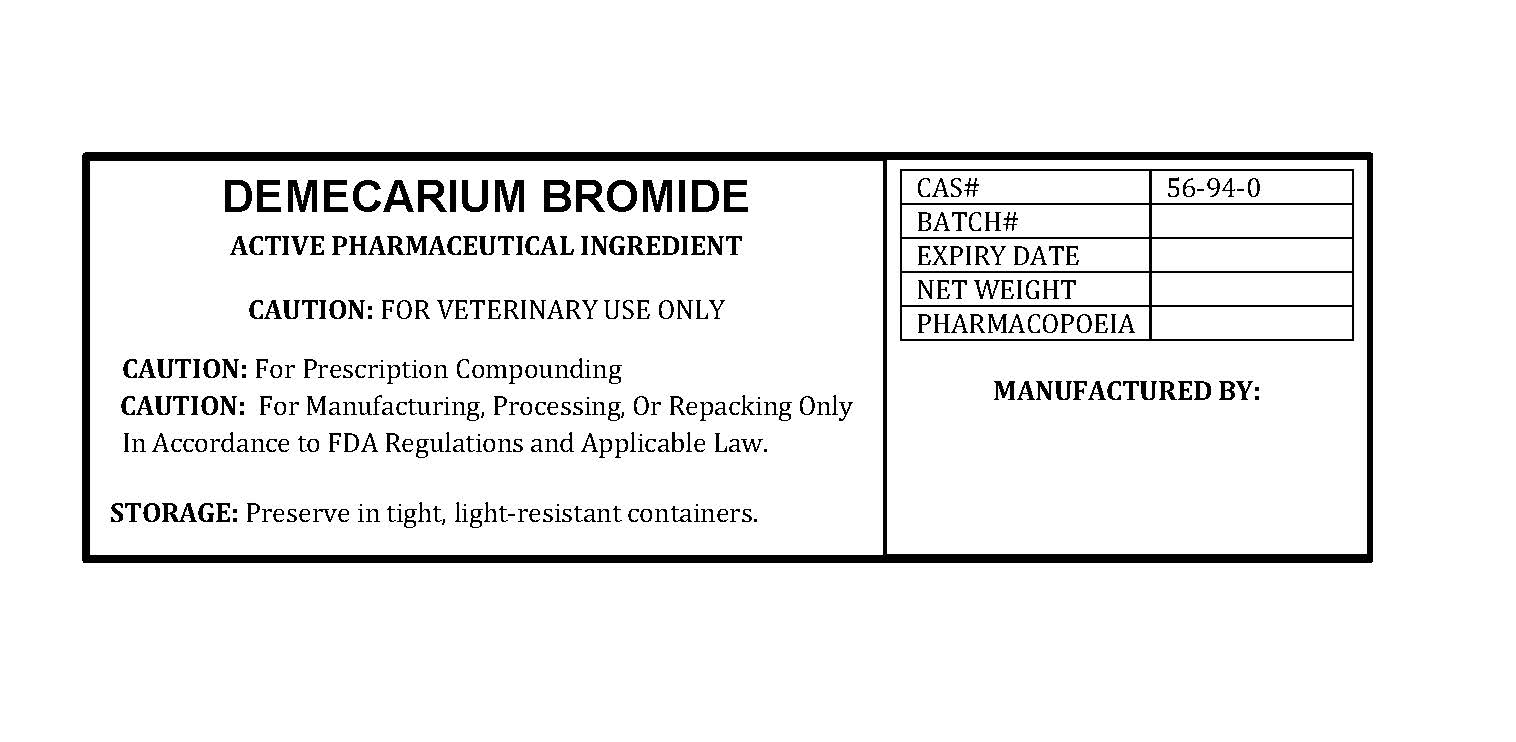 DRUG LABEL: DEMECARIUM BROMIDE
NDC: 86184-064 | Form: POWDER
Manufacturer: MAEDA INC
Category: other | Type: BULK INGREDIENT - ANIMAL DRUG
Date: 20250926

ACTIVE INGREDIENTS: DEMECARIUM BROMIDE 1 g/1 g

DEMECARIUM BROMIDE

PACKAGE LABEL

demecariumbromidelabelfile.jpg